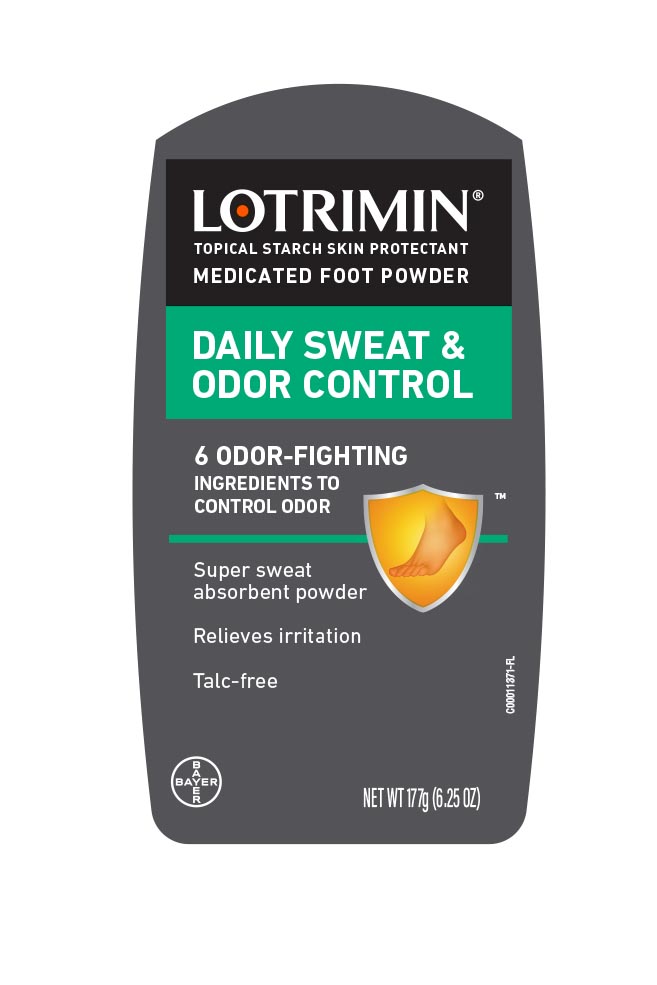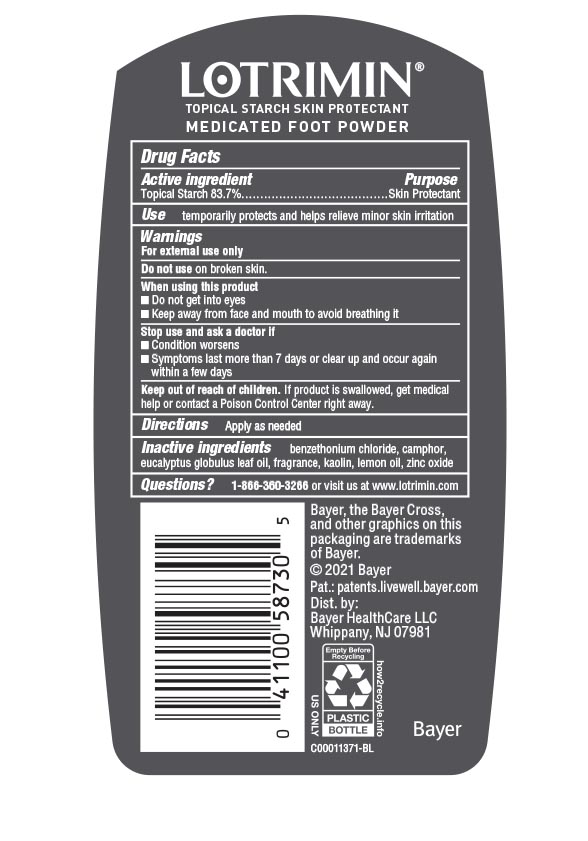 DRUG LABEL: Lotrimin Daily Sweat and Odor Control
NDC: 11523-0012 | Form: POWDER
Manufacturer: Bayer HealthCare LLC.
Category: otc | Type: HUMAN OTC DRUG LABEL
Date: 20260116

ACTIVE INGREDIENTS: STARCH, CORN 837 mg/1 g
INACTIVE INGREDIENTS: EUCALYPTUS OIL; BENZETHONIUM CHLORIDE; ZINC OXIDE; LEMON OIL; CAMPHOR (SYNTHETIC); KAOLIN

Lotrimin Daily Sweat and Odor Control Powder UI 1612345

Drug Facts

Active ingredient

Topical starch 83.7%

Purpose

Skin Protectant

Use

temporarily protects and helps relieve minor skin irritation

Warnings

For external use only

Do not use on broken skin.

When using this product

• Do not get into eyes

• Keep away from face and mouth to avoid breathing it

Stop use and ask a doctor if

- Condition worsens
- Symptoms last more than 7 days or clear up and occur again within a few days

Keep out of reach of children. If swallowed, get medical help or contact a Poison Control Center right away.

Directions

Apply as needed

Inactive ingredients

benzethonium chloride,camphor,eucalyptus globulus leaf oil, fragrance, kaolin,lemon oil, zinc oxide

Questions

Questions? 1-866-360-3266

Package display

LOTRIMIN

TOPICAL STARCH SKIN PROTECTANT

medicated foot powder

DAILY SWEAT

& ODOR CONTROL

6 odor-fighting

ingredients to control odor

- super sweat absorbent powder
- relieves irritation
- talc-free

NET WT 177 G (6.25 OZ)